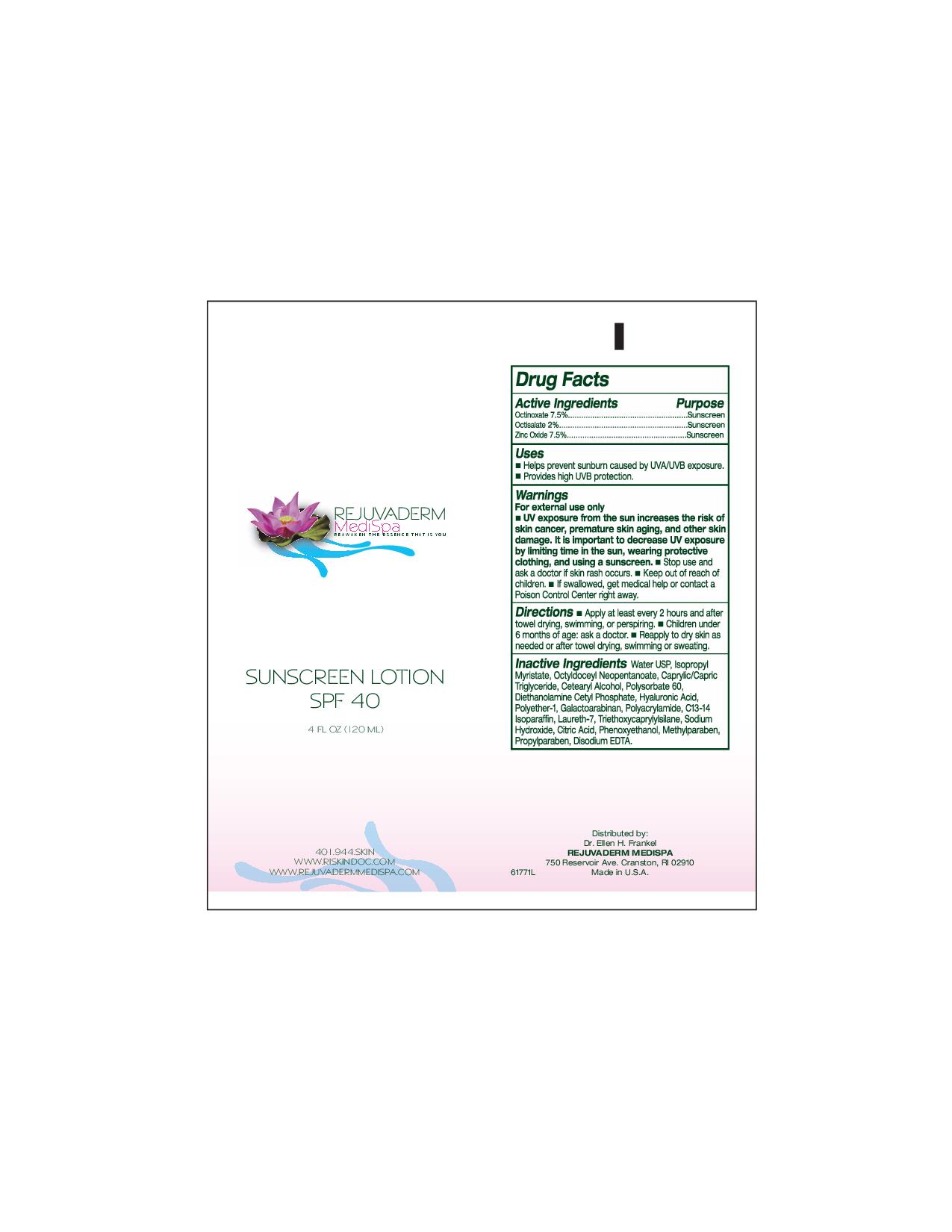 DRUG LABEL: Rejuvaderm Medispa sunscreen
NDC: 51325-100 | Form: LOTION
Manufacturer: Ellen H Frankle MD Inc
Category: otc | Type: HUMAN OTC DRUG LABEL
Date: 20100818

ACTIVE INGREDIENTS: Octinoxate 9 mL/120 mL; Octisalate 2.4 mL/120 mL; Zinc Oxide 9 mL/120 mL

Rejuvaderm Medispa Sunscreen

Active Ingredients Purpose

Octinoxate 7.5% Sunscreen

Octisalate 2% Sunscreen

Zinc Oxide 7.5% Sunscreen

Uses

- Helps prevent sunburn caused by UVA/UVB exposure
- Provides high UVB protection

Warnings

For external use only

- UV exposure from the sun increases the risk of skin cance, premature skin aging, and other skin damage. It is important to decrease UV exposure by limiting time in the sun, wearing protective clothing, and using a sunscreen.
- Stop use and ask a doctor if skin rash occurs.
- Keep out of reach of children.
- If swallowed, get medical help or contact a Poison Control Center right away.

Directions

- Apply at least every 2 hours and after towel drying, swimming, or perspiring
- Children under 6 months of age: ask a doctor
- Reapply to dry skin as needed or after towel drying, swimming or sweating.

Inactive Ingredients

Water USP, Isopropyl Myristate, Octyldoceyl Neopentanoate, Caprylic/Capric Triglyceride, Cetearyl alcohol, Polysorbate 60, Diethanolamine Cetyl Phosphate, Hyaluroic Acid, Polyether-1, Galactoarabinan, Polyacrylamide, C13-14 Isoparaffin, Laureth-7, Triethoxycaprlylsilane,Sodium Hydroxide, Citric Acid, Phenoxyethanol, Methylparaben, Propylparaben, Disodium EDTA.

PACKAGE LABEL

Rejuvaderm Medispa

Reawaken the essence that is you

Sunscreen Lotion SPF 40

4 fl oz (120 ml)

401.944skin

www.riskindoc.com

ww.rejuvadermmedispa.com